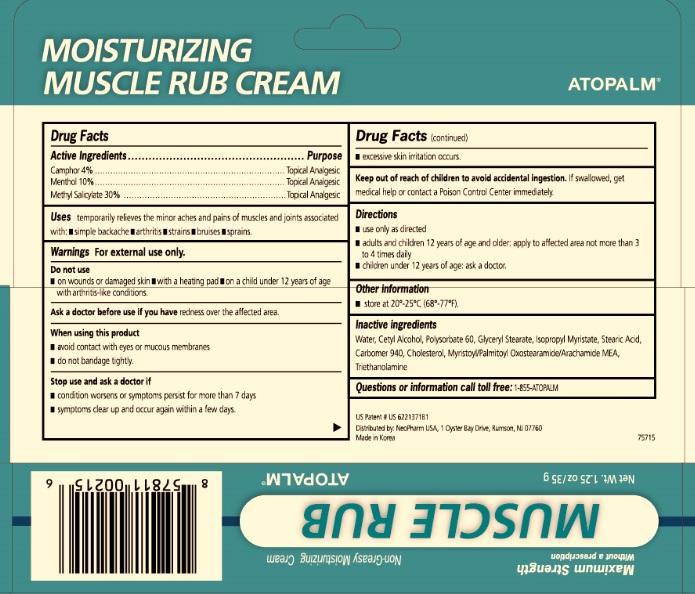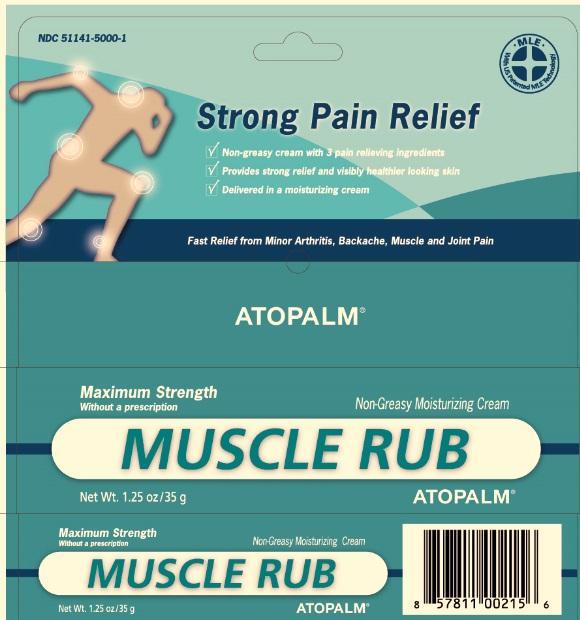 DRUG LABEL: ATOPALM MOISTURIZING MUSCLE RUB
                        
NDC: 51141-5000 | Form: CREAM
Manufacturer: NeoPharm Co., Ltd.
Category: otc | Type: HUMAN OTC DRUG LABEL
Date: 20150605

ACTIVE INGREDIENTS: CAMPHOR (SYNTHETIC) 4 g/100 g; MENTHOL 10 g/100 g; METHYL SALICYLATE 30 g/100 g
INACTIVE INGREDIENTS: WATER; CETYL ALCOHOL; POLYSORBATE 60; GLYCERYL MONOSTEARATE; ISOPROPYL MYRISTATE; STEARIC ACID; CARBOMER HOMOPOLYMER TYPE C; CHOLESTEROL; MYRISTOYL/PALMITOYL OXOSTEARAMIDE/ARACHAMIDE MEA; TROLAMINE

ATOPALM MOISTURIZING MUSCLE RUB CREAM

Drug Facts

Active Ingredients

Camphor 4%

Menthol 10%

Methyl Salicylate 30%

Purpose

Topical Analgesic

INDICATIONS AND USAGE

Uses temporarily relieves the minor aches and pains of muscles and joints associated with:

- simple backache
- arthritis
- strains
- bruises
- sprains

Warnings For external use only.

Do not use

- on wounds or damaged skin
- with a heating pad
- on a child under 12 years of age with arthritis-like conditions

Ask a doctor before use if you have redness over the affected area.

When using this product

- avoid contact with eyes or mucous membranes
- do not bandage tightly

Stop use and ask a doctor if

- condition worsens or symptoms persist for more than 7 days
- symptoms clear up and occur again within a few days
- excessive skin irritation occurs

Keep out of reach of children to avoid accidental ingestion. If swallowed, get medical help or contact a Poison Control Center immediately.

Directions

- use only as directed
- adults and children 12 years of age or older: apply to affected area not more than 3 to 4 times daily
- children under 12 years of age: ask a doctor

Other Information

- store at 20 degrees to 25 degrees (68 degrees to 77 degrees F)

Inactive Ingredients

Water, Cetyl Alcohol, Polysorbate 60, Glyceryl Stearate, Isopropyl Myristate, Stearic Acid, Carbomer 940, Cholesterol, Myristoyl/Palmitoyl Oxostearamide/Arachamide MEA, Triethanolamine

Questions? Call 1-855-ATOPALM

US Patent US 6221371B1

Distributed by: NeoPharm Co., Ltd, 80 Wood Rd, 212 Camarillo, CA 93010

Made in Korea

3 Pain Relievers

Moisturizing

Muscle Rub Cream

PACKAGE LABEL

Non-Greasy Cream

Three Pain Relieving Ingredients

With US Patented Technology

ATOPALM TM

MOISTURIZING MUSCLE RUB CREAM

WITH US PATENTED M L E TECHNOLOGY

Fast relief from Minor Arthritis, Backache, Muscle and Joint Pain

Provides Strong Relief and Visibly Healthier Looking Skin

Strong Pain Relief

Delivered in a Moisturizing Cream

ATOPALM TM

NON-GREASY CREAM WITH 3 PAIN RELIEVING INGREDIENTS

STRONG PAIN RELIEVING CREAM

Net Wt. 1.25 oz / 35 g